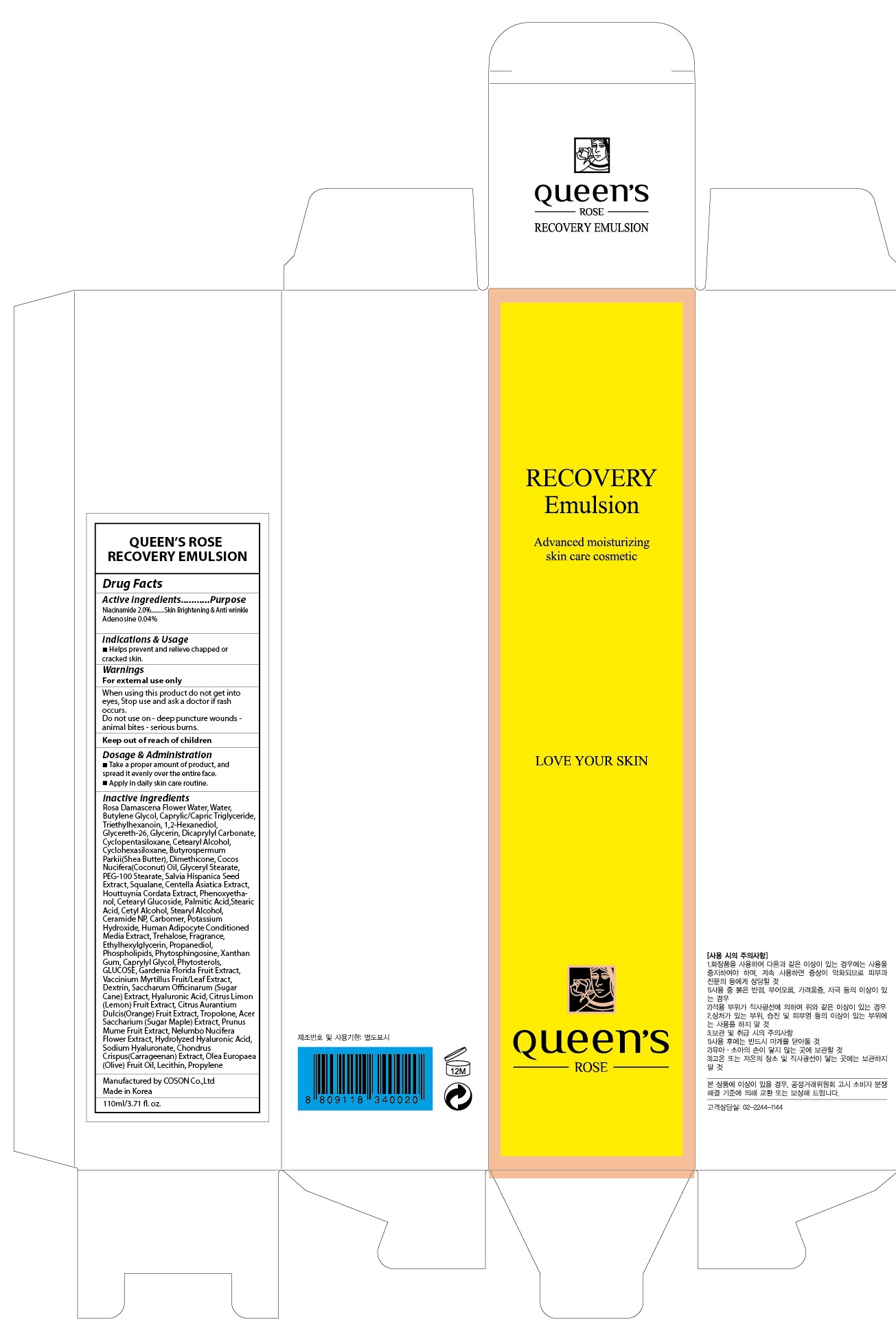 DRUG LABEL: QUEENS ROSE RECOVERY
NDC: 71252-020 | Form: EMULSION
Manufacturer: Cdpharmtec Co.,ltd
Category: otc | Type: HUMAN OTC DRUG LABEL
Date: 20170324

ACTIVE INGREDIENTS: Niacinamide 2.2 g/110 mL; Adenosine 0.044 g/110 mL
INACTIVE INGREDIENTS: ROSA DAMASCENA FLOWER OIL; Water

ACTIVE INGREDIENT

Active ingredients: Niacinamide 2.0%, Adenosine 0.04%

INACTIVE INGREDIENT

Inactive ingredients: Rosa Damascena Flower Water, Water, Butylene Glycol, Caprylic/Capric Triglyceride, Triethylhexanoin, 1,2-Hexanediol, Glycereth-26, Glycerin, Dicaprylyl Carbonate, Cyclopentasiloxane, Cetearyl Alcohol, Cyclohexasiloxane, Butyrospermum Parkii(Shea Butter), Dimethicone, Cocos Nucifera(Coconut) Oil, Glyceryl Stearate, PEG-100 Stearate, Salvia Hispanica Seed Extract, Squalane, Centella Asiatica Extract, Houttuynia Cordata Extract, Phenoxyethanol, Cetearyl Glucoside, Palmitic Acid,Stearic Acid, Cetyl Alcohol, Stearyl Alcohol, Ceramide NP, Carbomer, Potassium Hydroxide, Human Adipocyte Conditioned Media Extract, Trehalose, Fragrance, Ethylhexylglycerin, Propanediol, Phospholipids, Phytosphingosine, Xanthan Gum, Caprylyl Glycol, Phytosterols, GLUCOSE, Gardenia Florida Fruit Extract, Vaccinium Myrtillus Fruit/Leaf Extract, Dextrin, Saccharum Officinarum (Sugar Cane) Extract, Hyaluronic Acid, Citrus Limon (Lemon) Fruit Extract, Citrus Aurantium Dulcis(Orange) Fruit Extract, Tropolone, Acer Saccharium (Sugar Maple) Extract, Prunus Mume Fruit Extract, Nelumbo Nucifera Flower Extract, Hydrolyzed Hyaluronic Acid, Sodium Hyaluronate, Chondrus Crispus(Carrageenan) Extract, Olea Europaea (Olive) Fruit Oil, Lecithin, Propylene

PURPOSE

Purpose: Skin Brightening & Anti wrinkle

WARNINGS

Warnings: For external use only When using this product do not get into eyes, Stop use and ask a doctor if rash occurs. Do not use on - deep puncture wounds - animal bites - serious burns.

KEEP OUT OF REACH OF CHILDREN

INDICATIONS & USAGE

Indications & Usage: Helps prevent and relieve chapped or cracked skin.

DOSAGE & ADMINISTRATION

Dosage & Administration: - Take a proper amount of product, and spread it evenly over the entire face. - Apply in daily skin care routine.